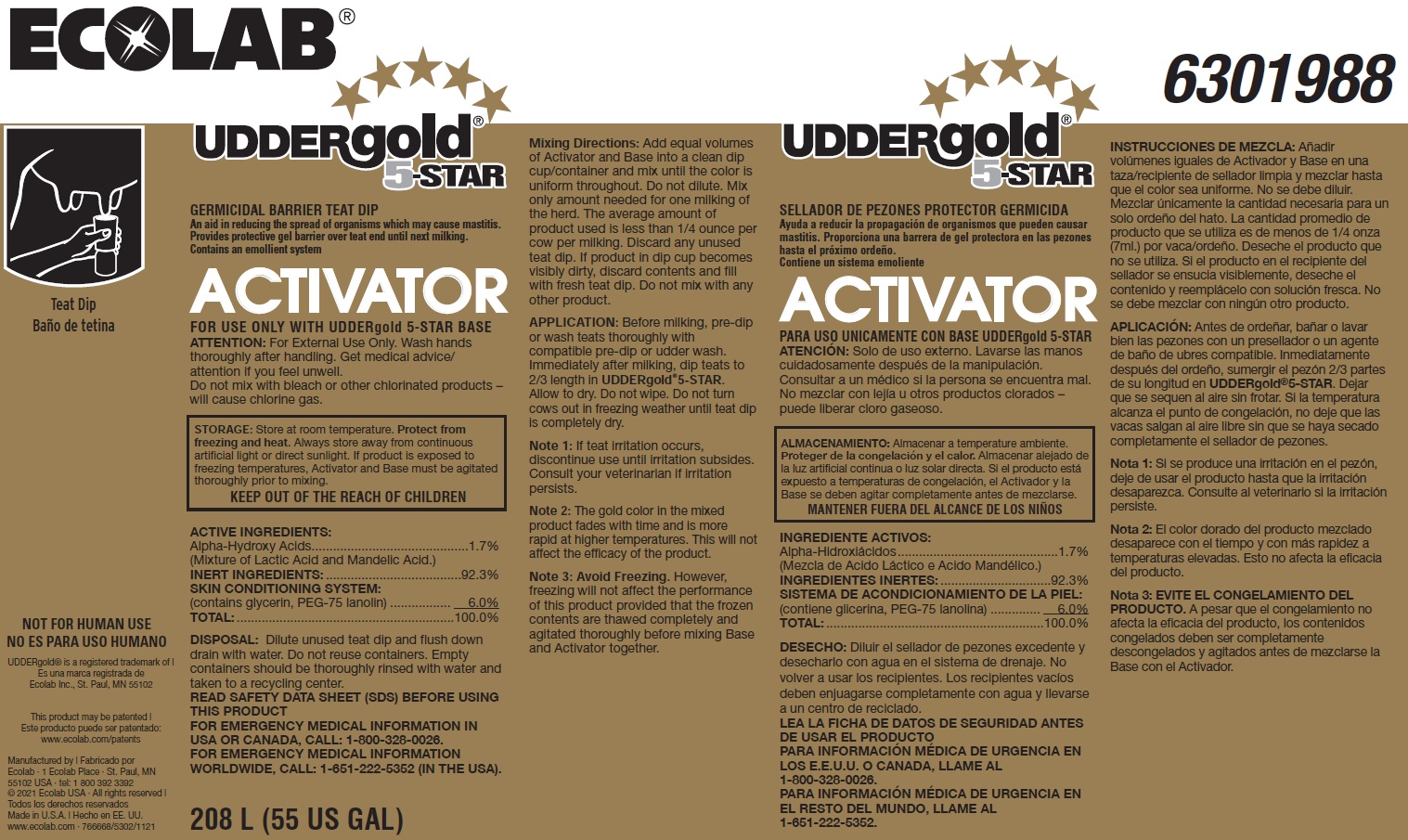 DRUG LABEL: Uddergold 5-Star Activator
NDC: 47593-609 | Form: SOLUTION
Manufacturer: Ecolab Inc.
Category: animal | Type: OTC ANIMAL DRUG LABEL
Date: 20251119

ACTIVE INGREDIENTS: LACTIC ACID 15 mg/1 mL; MANDELIC ACID 3 mg/1 mL
INACTIVE INGREDIENTS: GLYCERIN; PEG-75 LANOLIN; WATER

SAFE HANDLING WARNING

FOR USE ONLY WITH UDDERgold 5-STAR BASE

ATTENTION: For External Use Only. Wash hands thoroughly after handling. Get medical advice/

attention if you feel unwell.

Do not mix with bleach or other chlorinated products – will cause chlorine gas.

STORAGE: Store at room temperature. Protect from freezing and heat. Always store away from continuous artificial light or direct sunlight. If product is exposed to freezing temperatures, Activator and Base must be agitated thoroughly prior to mixing.

KEEP OUT OF THE REACH OF CHILDREN

NOT FOR HUMAN USE

DISPOSAL: Dilute unused teat dip and flush down drain with water. Do not reuse containers. Empty containers should be thoroughly rinsed with water and taken to a recycling center.

VETERINARY INDICATIONS

Mixing Directions: Add equal volumes of Activator and Base into a clean dip cup/container and mix until the color is uniform throughout. Do not dilute. Mix only amount needed for one milking of the herd. The average amount of product used is less than 1/4 ounce per cow per milking. Discard any unused teat dip. If product in dip cup becomes visibly dirty, discard contents and fill with fresh teat dip. Do not mix with any other product.

APPLICATION: Before milking, pre-dip or wash teats thoroughly with compatible pre-dip or udder wash. Immediately after milking, dip teats to 2/3 length in UDDERgold®5-STAR. Allow to dry. Do not wipe. Do not turn cows out in freezing weather until teat dip is completely dry.

Note 1: If teat irritation occurs, discontinue use until irritation subsides. Consult your veterinarian if irritation persists.

Note 2: The gold color in the mixed product fades with time and is more rapid at higher temperatures. This will not affect the efficacy of the product.

Note 3: Avoid Freezing. However, freezing will not affect the performance of this product provided that the frozen contents are thawed completely and agitated thoroughly before mixing Base and Activator together.

OTHER SAFETY INFORMATION

READ SAFETY DATA SHEET (SDS) BEFORE USING THIS PRODUCT

FOR EMERGENCY MEDICAL INFORMATION IN USA OR CANADA, CALL: 1-800-328-0026.

FOR EMERGENCY MEDICAL INFORMATION WORLDWIDE, CALL: 1-651-222-5352 (IN THE USA).

Representative label and principal display panel

ECOLAB 6301988

UDDERGOLD 5-STAR

GERMICIDAL BARRIER TEAT DIP

An aid in reducing the spread of organisms which may cause mastitis.

Provides protective gel barrier over teat end until next milking.

Contains an emollient system

ACTIVATOR

ACTIVE INGREDIENTS:

Alpha-Hydroxy Acids............................................1.7%

(Mixture of Lactic Acid and Mandelic Acid.)

INERT INGREDIENTS: ......................................92.3%

SKIN CONDITIONING SYSTEM:

(contains glycerin, PEG-75 lanolin) ................. 6.0%

TOTAL: .............................................................100.0%

208 L (55 US GAL)

Manufactured by | Fabricado por

Ecolab · 1 Ecolab Place · St. Paul, MN

55102 USA · tel: 1 800 392 3392

© 2021 Ecolab USA · All rights reserved |

Todos los derechos reservados

Made in U.S.A. | Hecho en EE. UU.

www.ecolab.com · 766668/5302/1121